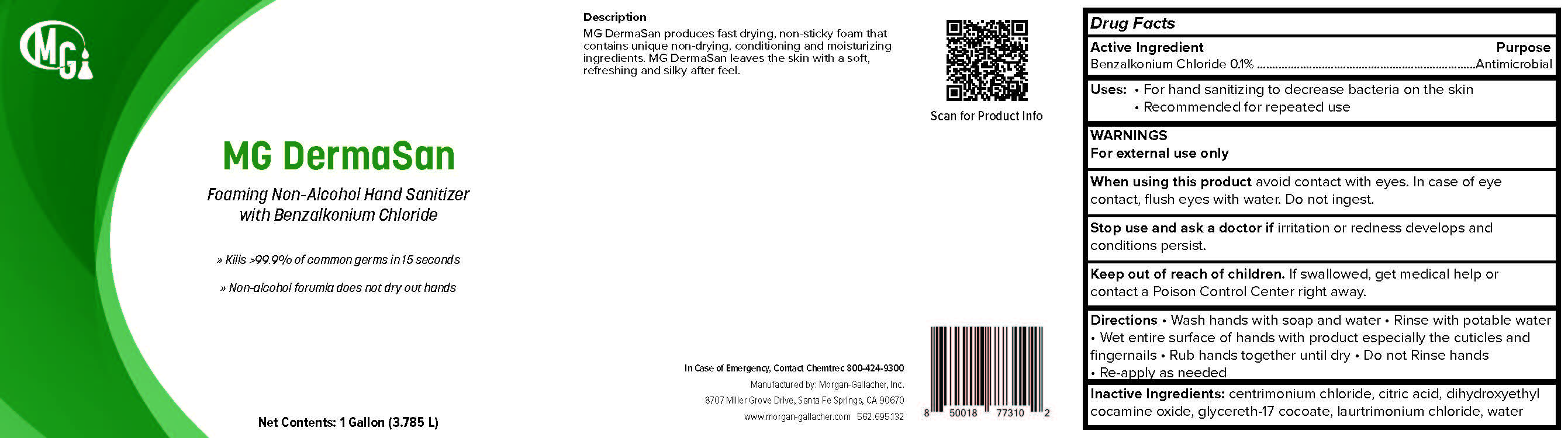 DRUG LABEL: MG DermaSan
NDC: 50241-259 | Form: LIQUID
Manufacturer: Morgan Gallacher Inc.
Category: otc | Type: HUMAN OTC DRUG LABEL
Date: 20251223

ACTIVE INGREDIENTS: BENZALKONIUM CHLORIDE 0.1 g/100 g
INACTIVE INGREDIENTS: WATER; CETRIMONIUM CHLORIDE; LAURTRIMONIUM CHLORIDE; DIHYDROXYETHYL COCAMINE OXIDE; GLYCERETH-17 COCOATE; CITRIC ACID MONOHYDRATE

MG DermaSan

Active Ingredient

Benzalkonium Chloride.........0.1 %

Uses

- For hand sanitizing to decrease bacteria on the skin
- Recommended for repeated use

Purpose

Antimicrobial

Warnings

- For external use only.
- When using this product avoid contact with eyes. In case of eye contact, flush eyes with water. Do not ingest.
- Stop use and ask a doctor if irritation or redness develops and conditions persist.

Keep out of reach of children. If swallowed, get medical help or contact a Poison Conrol Center right away

Directions

- Pump a small amount of foam into palm of hand.
- Rub thoroughly over all surfaces of both hands.
- Rub hands together briskly until dry.

Inert Ingredients

- water
- cetrimonium chloride
- laurtrimonium chloride
- dihydroxyethyl cocamine oxide
- glycereth-17 cocoate
- citric acid